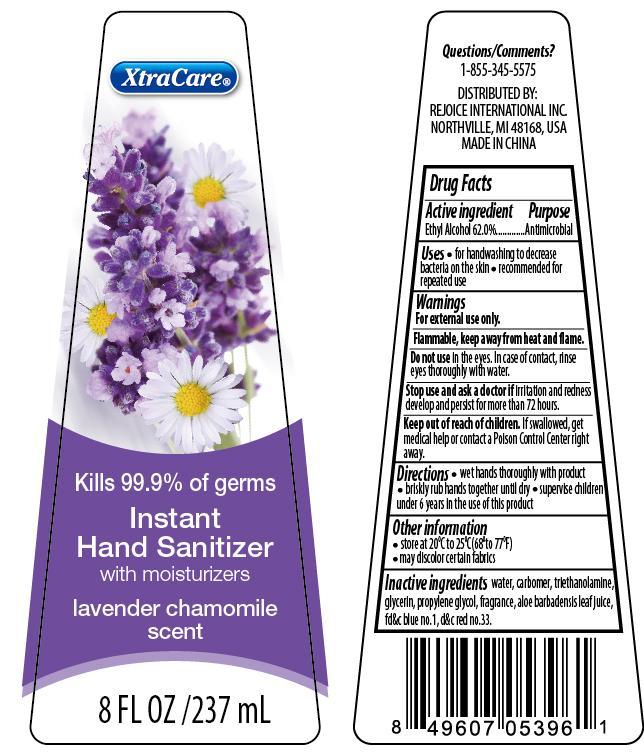 DRUG LABEL: XtraCare Lavender Chamomile
NDC: 57337-072 | Form: GEL
Manufacturer: Rejoice International
Category: otc | Type: HUMAN OTC DRUG LABEL
Date: 20250212

ACTIVE INGREDIENTS: ALCOHOL 62 g/100 g
INACTIVE INGREDIENTS: WATER; CARBOMER COPOLYMER TYPE A; TROLAMINE; GLYCERIN; PROPYLENE GLYCOL; ALOE VERA LEAF; FD&C BLUE NO. 1; D&C RED NO. 33

XtraCare Lavender Chamomile

Active Ingredient Purpose

Ethyl Alcohol 62.0% ................. Antimicrobial

Uses

- for handwashing to decrease bacteria on the skin
- recommended for repeated use

Keep out of reach of children. If swallowed, get medical help or contact a poison control center right away.

INDICATIONS AND USAGE

XtraCare®
Kills 99.9% of germs
Instant Hand Sanitizer
with moisturizers
cucumber melon scent
8 FL OZ / 237 mL

Directions

- wet hands thoroughly with product
- briskly rub hands together until dry
- supervise children under 6 years in the use of this product

Warnings

For external use only

Flammable, keep away from heat and flame.

Do not use in the eyes. In case of contact, rinse eyes thoroughly with water.

Stop use and ask a doctor if irritation and redness develop and persist for more than 72 hours.

Inactive Ingredients

water, carbomer, triethanolamine, glycerin, propylene glycol, fragrance, aloe barbadensis leaf juice, fd&c blue no. 1, fd&c red no.33